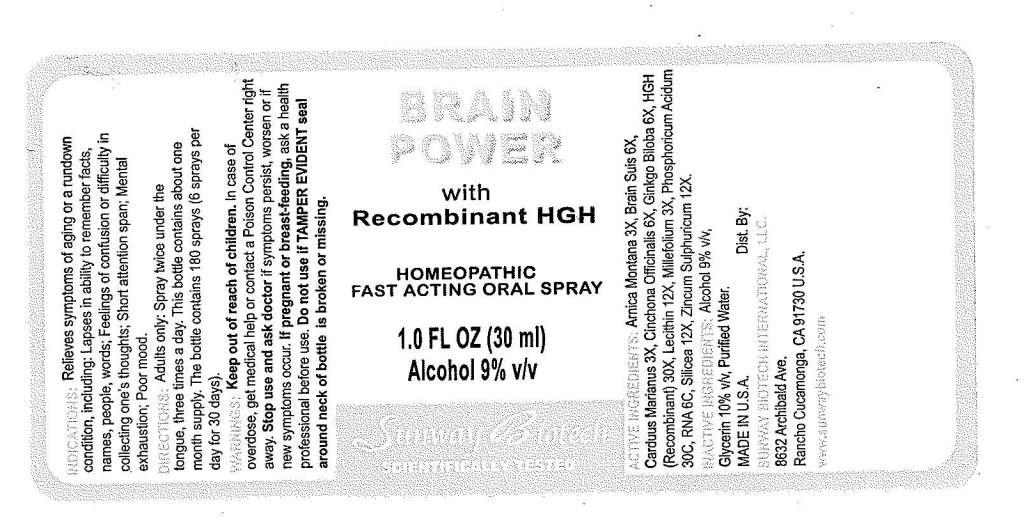 DRUG LABEL: Brain Power
NDC: 50845-0056 | Form: SPRAY
Manufacturer: Liddell Laboratories, Inc.
Category: homeopathic | Type: HUMAN OTC DRUG LABEL
Date: 20110615

ACTIVE INGREDIENTS: ARNICA MONTANA 3 [hp_X]/1 mL; PORK BRAIN 6 [hp_X]/1 mL; SILYBUM MARIANUM SEED 3 [hp_X]/1 mL; CINCHONA OFFICINALIS BARK 6 [hp_X]/1 mL; GINKGO 6 [hp_X]/1 mL; SOMATROPIN 30 [hp_X]/1 mL; LECITHIN, SOYBEAN 12 [hp_X]/1 mL; ACHILLEA MILLEFOLIUM 3 [hp_X]/1 mL; PHOSPHORIC ACID 30 [hp_C]/1 mL; SILICON DIOXIDE 12 [hp_X]/1 mL; ZINC SULFATE HEPTAHYDRATE 12 [hp_X]/1 mL; SACCHAROMYCES CEREVISIAE RNA 6 [hp_C]/1 mL
INACTIVE INGREDIENTS: WATER; ALCOHOL; GLYCERIN

Brain Power

ACTIVE INGREDIENT

ACTIVE INGREDIENTS: Arnica montana 3X, Brain suis 6X, Carduus marianus 3X, Cinchona officinalis 6X, Ginkgo biloba 6X, HGH 30X, Lecithin 12X, Millefolium 3X, Phosphoricum acidum 30C, RNA 6C, Silicea 12X, Zincum sulphuricum 12X.

PURPOSE

INDICATIONS: Relieves symptoms of aging or a rundown condition, including: Lapses in ability to remember facts, names, people, words; Feeling of confusion or difficulty in collecting one's thoughts; Short attention span; Mental exhaustion; Poor mood.

WARNINGS

WARNINGS: Keep out of reach of children. In case of overdose, get medical help or contact a Poison Control Center right away.

Stop use and ask doctor is symptoms persist, worsen or if new symptoms occur.

If pregnant or breast-feeding, ask a health professional before use.

Do not use if TAMPER EVIDENT seal around neck of bottle is broken or missing.

DOSAGE AND ADMINISTRATION

DIRECTIONS: Adults only: Spray twice under the tongue, three times a day. This bottle contains about one month supply. The bottle contains 180 sprays (6 sprays per day for 30 days).

INACTIVE INGREDIENT

INACTIVE INGREDIENTS: Alcohol 9% v/v, Glycerin 10% v/v. Purified water.

KEEP OUT OF REACH OF CHILDREN. In case of overdose, get medical help or contact a Poison Control Center right away.

INDICATIONS AND USAGE

INDICATIONS: Relieves symptoms of aging or a rundown condition, including: Lapses in ability to remember facts, names, people, words; Feelings of confusion or difficulty in collecting one's thoughts; Short attention span; Mental exhaustion; Poor mood.

QUESTIONS

MADE IN U.S.A.

Dist. By:

SUNWAY BIOTECH INTERNATIONAL, LLC

8632 Archibald Ave.

Rancho Cucamonga, CA 91730

www.sunwaybiotech.com

PACKAGE LABEL

BRAIN POWER

with

Recombinant HGH

HOMEOPATHIC

FAST ACTING ORAL SPRAY

1.0 FL OZ (30 ML)

SUNWAY BIOTECH

SCIENTIFICALLY TESTED